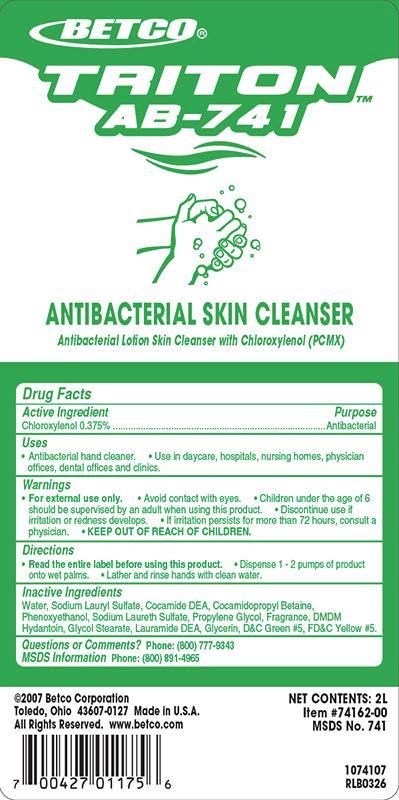 DRUG LABEL: Triton AB-741
NDC: 65601-741 | Form: SOAP
Manufacturer: Betco Corporation, Ltd.
Category: otc | Type: HUMAN OTC DRUG LABEL
Date: 20121112

ACTIVE INGREDIENTS: CHLOROXYLENOL 3.75 mg/1 mL
INACTIVE INGREDIENTS: WATER; SODIUM LAURYL SULFATE; COCO DIETHANOLAMIDE; COCAMIDOPROPYL BETAINE; PHENOXYETHANOL; PROPYLENE GLYCOL; DMDM HYDANTOIN; GLYCOL STEARATE; LAURIC DIETHANOLAMIDE; GLYCERIN; D&C GREEN NO. 5; FD&C YELLOW NO. 5

Triton AB-741

Triton AB-741

Active Ingredient

Chloroxylenol 0.375%

Triton AB-741

Uses

- Antibacterial hand cleaner.
- Use in daycare, hospitals, nursing homes, physicians offices, dental offices and clinics

Triton AB-741

Warnings

- For external use only.
- Avoid contact with eyes.
- Children under the age of 6 should be supervised by an adult when using this product.
- Discontinue use is irritation or redness develops.
- If irritation persists for more than 72 hours, consult a physician.
- KEEP OUT OF REACH OF CHILDREN.

Triton AB-741

Directions

- Read the entire label before using this product.
- Dispense 1-2 pumps of product onto wet palm.
- Lather and rinse hands with clean water

Triton AB-741

Inactive Ingredients

Water, Sodium Lauryl lSulfate, Cocamide DEA, Cocamidopropyl betadine, Phenoxyethanol, Sodium Laureth Sulfate, Propylene Glycol, Fragrance, DMDM Hydantoin, Glycol Stearate, Laurimide DEA, Glycerine, Tocopheryl Acetate, D&C Green #5, FD&C Yellow #5.

Triton AB-741

Questions or Comments? Phone: (800) 777-9343

MDS information:(800) 891-4965

Triton AB-741

Purpose

Antibacterial

Triton AB-741

Winning Hands Antibacterial

KEEP OUT OF REACH OF CHILDREN

Triton AB-741

Antibacterial Skin Cleanser

Antibacterial Lotion Skin Cleanser with Chloroxylenol (PCMX)

Net Contents: 2 L

Item #: 74162-00

MSDS No.:741

2007 Betco Corproration

Toledo Ohio 43607-0127 Made in the U.S.A.

All Rights Reserved. www.betco.com